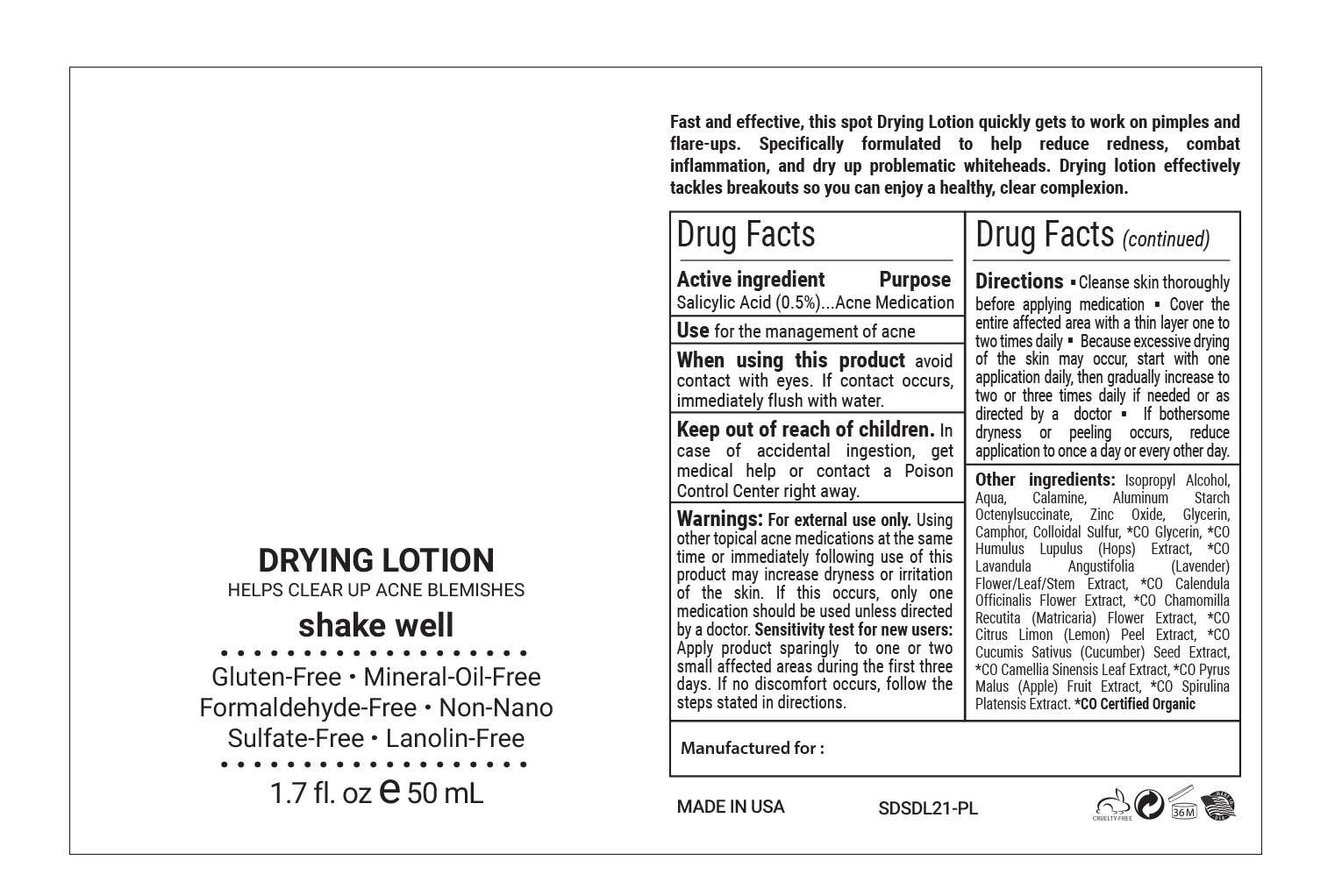 DRUG LABEL: Acne Drying
NDC: 68062-9003 | Form: LOTION
Manufacturer: Spa de Soleil
Category: otc | Type: HUMAN OTC DRUG LABEL
Date: 20210915

ACTIVE INGREDIENTS: SALICYLIC ACID 1 g/50 mL
INACTIVE INGREDIENTS: ALUMINUM STARCH OCTENYLSUCCINATE; ISOPROPYL ALCOHOL; WATER

Acne Drying Lotion

Active ingredient Purpose

Salicylic Acid (0.5%)..........Acne Medication

Purpose

Acne Medication

INDICATIONS AND USAGE

Use for the management of acne

WARNINGS

Warnings: For external use only. Using other topical acne medications at the same time or immediately following use of this product may increase dryness or irritation of the skin. If this occurs, only one medication should be used unless directed by a doctor. Sensitivity test for new users: Apply product sparingly to one or two small affected areas during the first three days. If no discomfort occurs, follow the steps stated in directions.

Keep out of reach of children. In case of accidental ingestion, get medical help or contact a Poison Control Center right away.

DOSAGE AND ADMINISTRATION

Directions: Cleanse skin thoroughly before applying medication . Cover the entire affected area with a thin layer one to two times daily. Because excessive drying of the skin may occur, start with one application daily, then gradually increase to two or three times daily if needed or as directed by a doctor . If bothersome dryness or peeling occurs, reduce application to once a day or every other day.

INACTIVE INGREDIENT

Other ingredients: Isopropyl Alcohol, Aqua, Calamine, Aluminum Starch Octenylsuccinate, Zinc Oxide, Glycerin, Camphor, Colloidal Sulfur, *CO Glycerin, *CO Humulus Lupulus (Hops) Extract, *CO Lavandula Angustifolia (Lavender) Flower/Leaf/Stem Extract, *CO Calendula Officinalis Flower Extract, *CO Chamomilla Recutita (Matricaria) Flower Extract, *CO Citrus Limon (Lemon) Peel Extract, *CO Cucumis Sativus (Cucumber) Seed Extract, *CO Camellia Sinensis Leaf Extract, *CO Pyrus Malus (Apple) Fruit Extract, *CO Spirulina Platensis Extract.

*CO Certified Organic